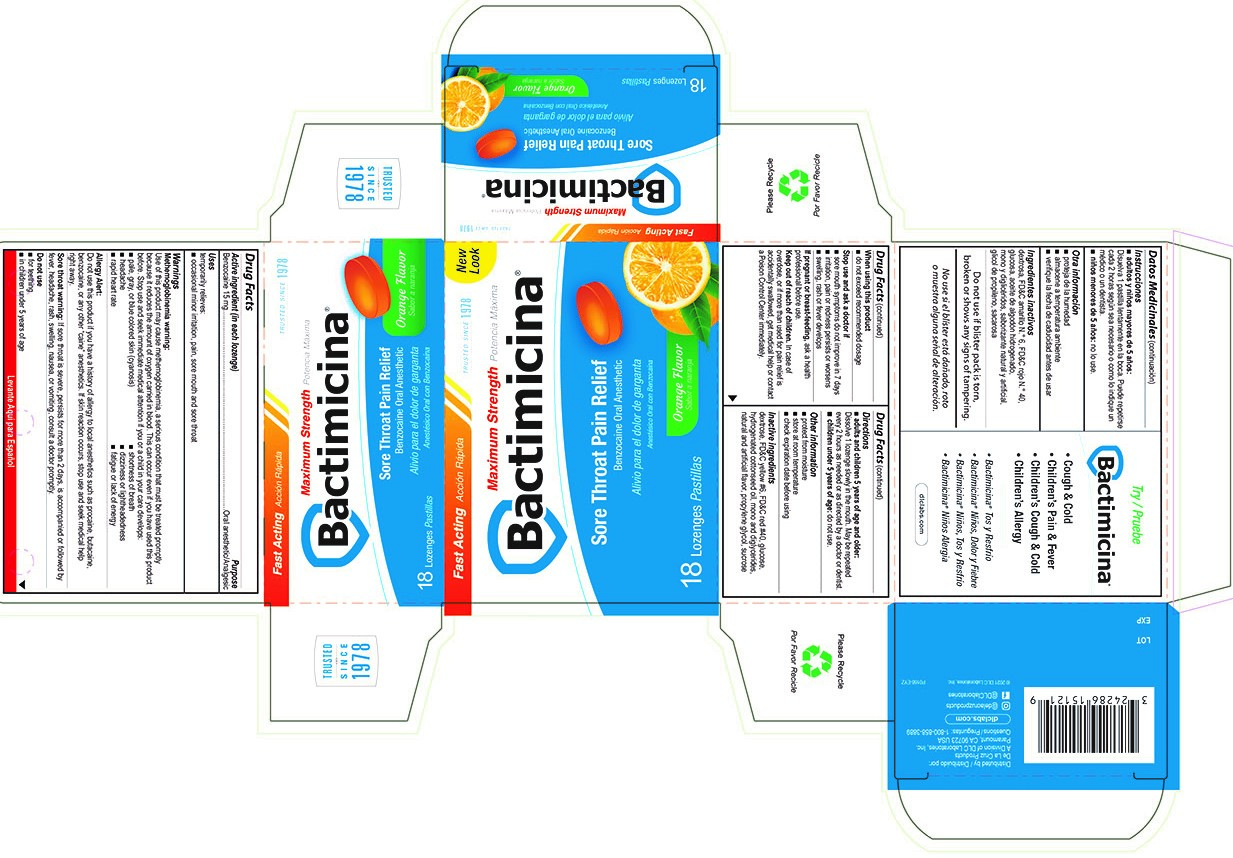 DRUG LABEL: Bactimicina for Sore Throat
NDC: 24286-1577 | Form: LOZENGE
Manufacturer: DLC Laboratories, Inc.
Category: otc | Type: HUMAN OTC DRUG LABEL
Date: 20240710

ACTIVE INGREDIENTS: BENZOCAINE 15 mg/1 1
INACTIVE INGREDIENTS: FD&C RED NO. 40; PROPYLENE GLYCOL; SUCROSE; HYDROGENATED COTTONSEED OIL; FD&C YELLOW NO. 6; DEXTROSE; CORN SYRUP

Bactimicina Lozenge

Active Ingredient (in each lozenge)

Benzocaine 15 mg

Purpose

Oral anesthetic/Analgesic

Use

temporarily relieve:

- occational minor irritation, pain, sore mouth and sore throat

Warnings

Methemoglobinemia warning:

Use of this product may cause methemoglobinemia, a serious condition that must be treated promptly because it reduces the amount of oxygen carried in blood. This can occur even if you have used this product before. Stop use and seek immediate medical attention if you or a child in your care developes:

- pale, gray, or blue colored skin (cyanosis)
- shortness of breath
- headache
- dizziness or lightheadedness
- rapid heart rate
- fatigue or lack of energy

Allergy Alert

Do not use this product if you have a history of allergy to local anesthetics such as procaine, butacaine, benzocaine, or any other "caine" anesthetics. If skin reation occurs, stop use and seek medical help right away.

Sore throat warning:

If sore throat is severe, persists for more than 2 days, is accompanied or followed by fever, headache, rash, swelling, nausea, or vomiting, consult a doctor promptly.

Do not use

- for teething
- in children under 5 years of age

When using this product

- do not exceed recommended dosage

Stop use and ask a doctor if

- sore mouth symptoms do not improve in 7 days
- irritation, pain or redness persists or worsens
- swelling, rash or fever develops

If pregnant or breast-feeding

ask a health professional before use

Keep out of reach of children

In case of overdose, or if more than used for pain relief is accidentally swallowed, get medical help or contact a Poison COntrol Center immediately

Directions

- adults and children 5 years of age and older:

Dissolve 1 lozenge slowly in the mouth. May be repeated every 2 hours as needed or as directed by a doctor or dentist.

- children under 5 years of age: do not use.

Other information

- protect from moisture
- store at room temperature
- check expiration date before using

Inactive Ingredients

dextrose, FD&C yellow #6, FD&C red #40, corn syrup, hydrogenated cottonseed oil, natural and artificial flavor, propylene glycol, sucrose

Question

1-800-858-3889

Distributed by

De La Cruz Products

A Division of DLC Laboratories, Inc.

Paramount, CA 90723 USA

Principle Display

Fast Acting

Trusted since 1978

New Look

Maximum Strength

Bactimicina ®

Sore Throat Pain Relief

Benzocain Oral Anesthetic

Orange Flavor

18 Lozenges